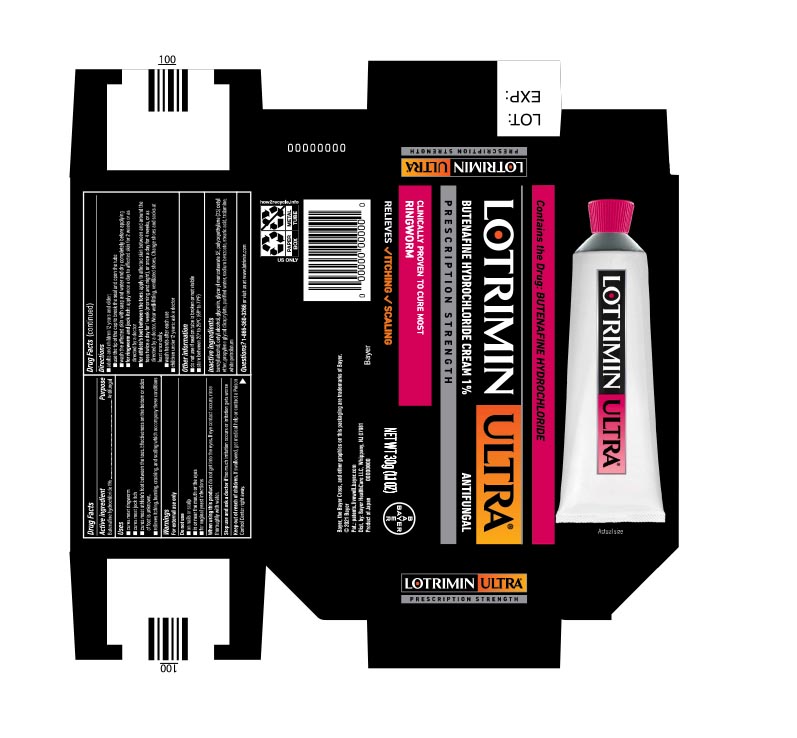 DRUG LABEL: Lotrimin Ultra
NDC: 11523-0158 | Form: CREAM
Manufacturer: Bayer Healthcare LLC.
Category: otc | Type: HUMAN OTC DRUG LABEL
Date: 20251204

ACTIVE INGREDIENTS: BUTENAFINE HYDROCHLORIDE 1 g/100 g
INACTIVE INGREDIENTS: BENZYL ALCOHOL; CETYL ALCOHOL; GLYCERIN; CETETH-23; PROPYLENE GLYCOL DICAPRYLATE; WATER; SODIUM BENZOATE; STEARIC ACID; TROLAMINE; PETROLATUM

Lotrimin Ultra
Ringworm

Drug Facts

Active ingredient

Butenafine hydrochloride 1%

Purpose

Antifungal

Uses

- cures most ringworm
- cures most jock itch
- cures most athlete's foot between the toes. Effectiveness on the bottom or sides of foot is unknown.
- relieves itching, burning, cracking, and scaling which accompany these conditions

Warnings

For external use only

Do not use

- on nails or scalp
- in or near the mouth or the eyes
- for vaginal yeast infections

When using this product do not get into the eyes. If eye contact occurs, rinse thoroughly with water.

Stop use and ask a doctor if too much irritation occurs or irritation gets worse

Keep out of reach of children. If swallowed, get medical help or contact a Poison Control Center right away.

Directions

adults and children 12 years and older:

- use the tip of the cap to break the seal and open the tube
- wash the affected skin with soap and water and dry completely before applying
- for ringworm and jock itch: apply once a day to affected skin for 2 weeks or as directed by a doctor
- for athlete's foot between the toes: apply to affected skin between and around the toes twice a day for 1 week (morning and night), or once a day for 4 weeks, or as directed by a doctor. Wear well-fitting, ventilated shoes. Change shoes and socks at least once daily.
- wash hands after each use

children under 12 years: ask a doctor

Other information

- do not use if seal on tube is broken or not visible
- store between 20° to 25°C (68° to 77°F)

Inactive ingredients

benzyl alcohol, cetyl alcohol, glycerin, glyceryl monostearate SE, polyoxyethylene (23) cetyl ether, propylene glycol dicaprylate, purified water, sodium benzoate, stearic acid, trolamine, white petrolatum

Questions?

Questions? 1-866-360-3266 or visit us a www.lotrimin.com